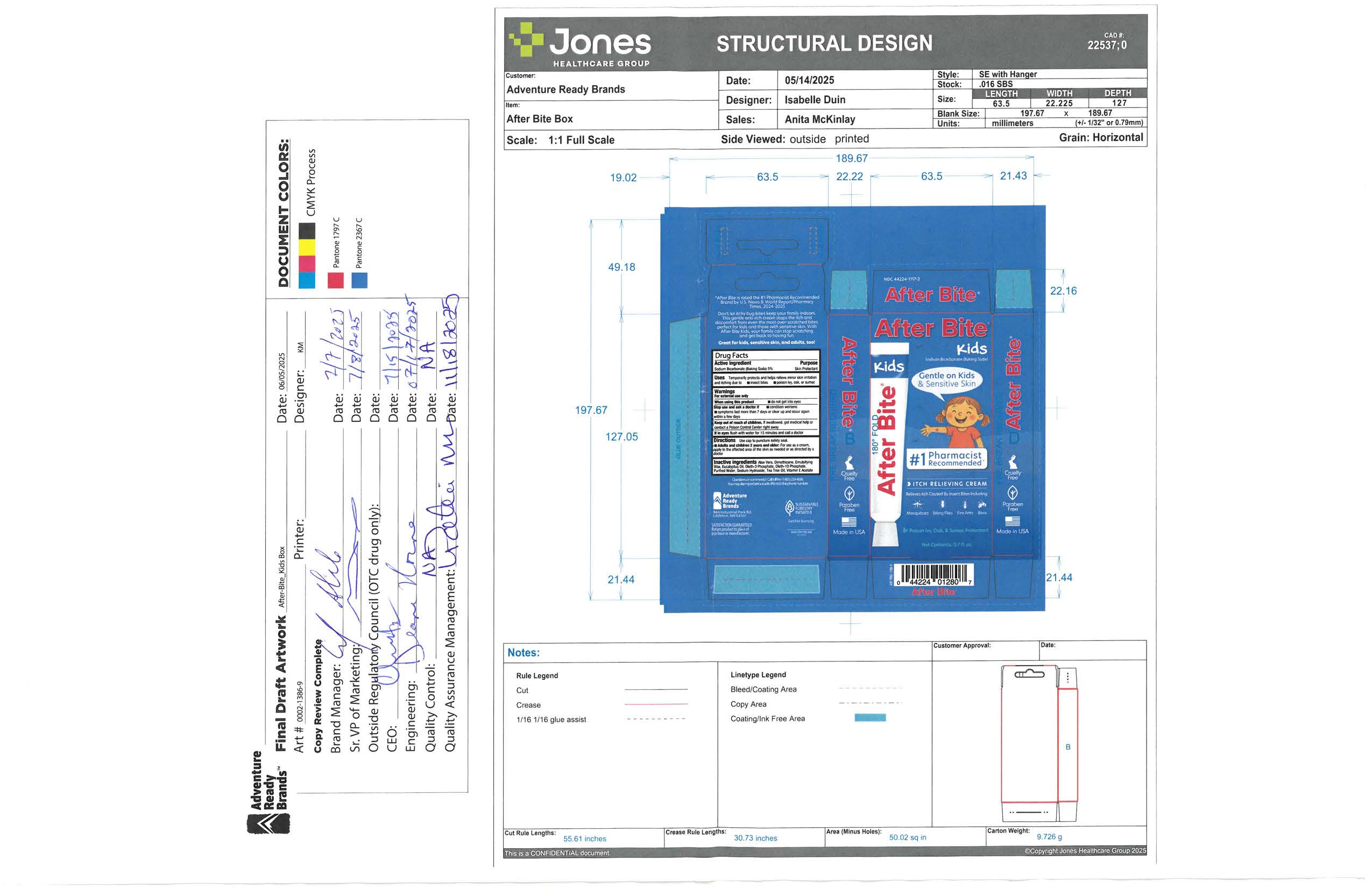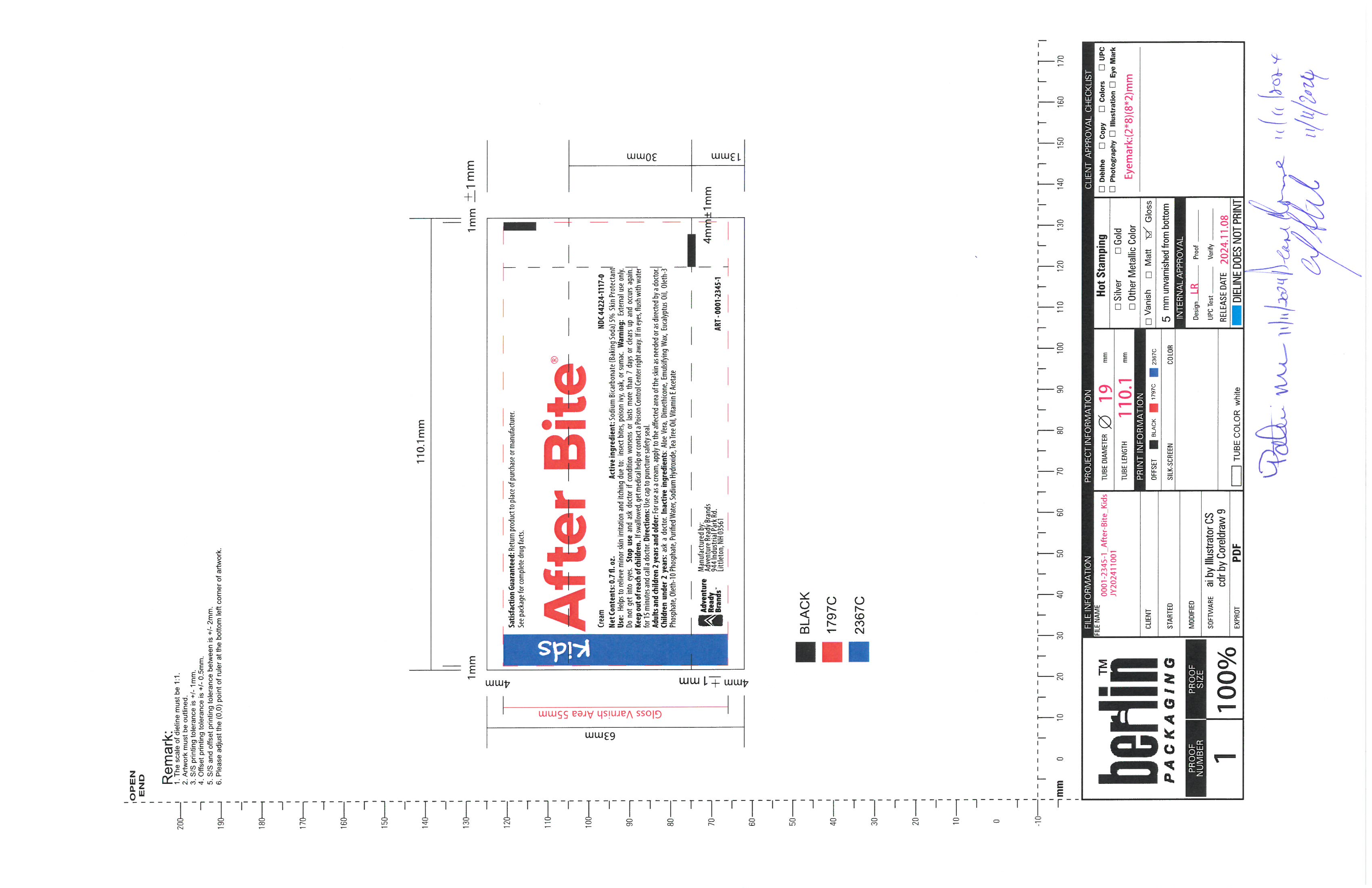 DRUG LABEL: After Bite Kids
NDC: 44224-1117 | Form: CREAM
Manufacturer: Tender Corporation d/b/a Adventure Ready Brands
Category: otc | Type: HUMAN OTC DRUG LABEL
Date: 20251118

ACTIVE INGREDIENTS: SODIUM BICARBONATE 1.04 g/20 g
INACTIVE INGREDIENTS: WHITE WAX 2 g/20 g; .ALPHA.-TOCOPHEROL ACETATE 0.1 g/20 g; SODIUM HYDROXIDE 0.33 g/20 g; EUCALYPTUS OIL 0.26 g/20 g; ALOE VERA LEAF 1.1 g/20 g; OLETH-10 PHOSPHATE 0.28 g/20 g; OLETH-3 PHOSPHATE 0.5 g/20 g; WATER 14.1 g/20 g; TEA TREE OIL 0.2 g/20 g; DIMETHICONE 350 0.1 g/20 g

After Bite Kids

Active Ingredients

Sodium Bicarbonate (Baking Soda) 5%

Purpose

Skin protectant

Uses

Temprarily protects and helps relieve minor skin irritation and itching due to, insect bites, poison ivy, oak, or sumac

Warnings

For external use only

When using this product

do not get into eyes

Stop use and ask a doctor if

Conditions worsen, symptoms last more than 7 days or clears up and occur again within a few days.

Keep out of reach of children

if swallowed, get medical help or contact poison control center right away

If in eyes

Flush with water for 15 minutes and call a doctor

Directions

Use cao to puncture safety seal.

Adults and children 2 years and older: for use as a cream apply to affected area of the skin as needed or directed by a doctor.

Inactive ingredients

aloe vera, dimethicone,emulsifying wax, eucalyptus oil, oleth-3 phosphate, oleth-10 phosphate, pourified water, sodium hydroxide, tea tree oil, vitamine e acetate